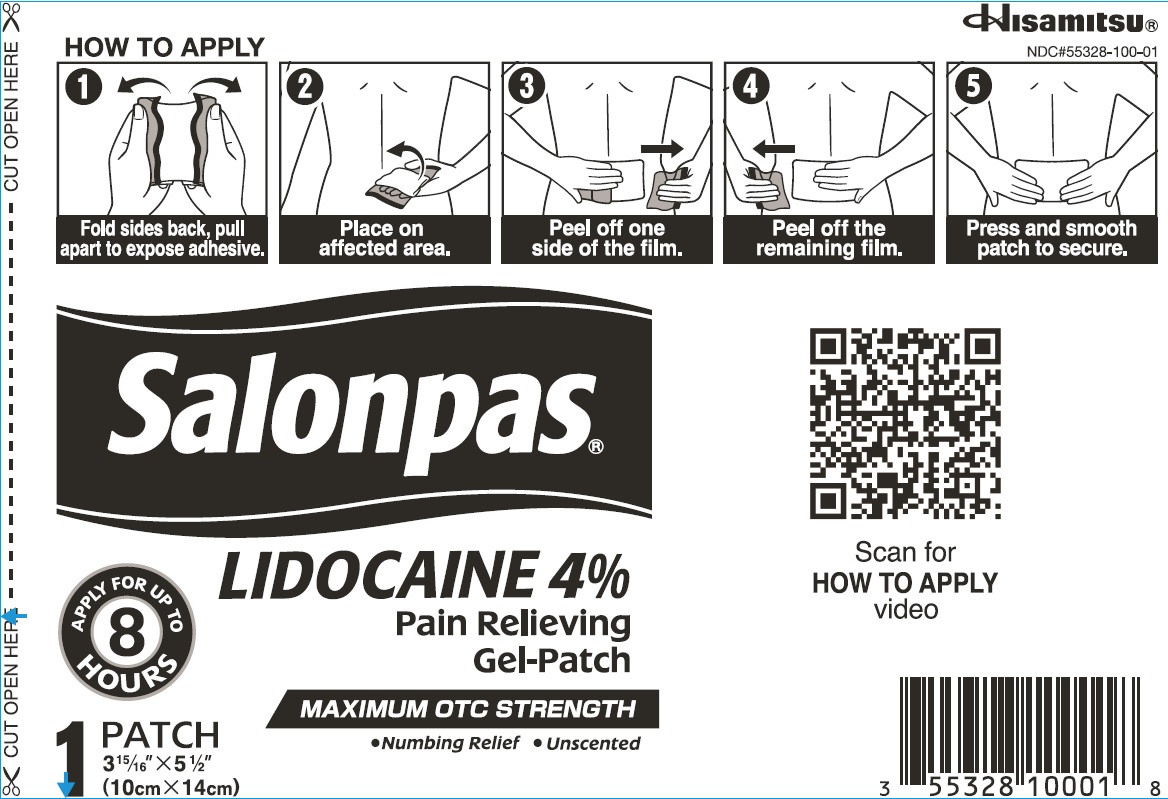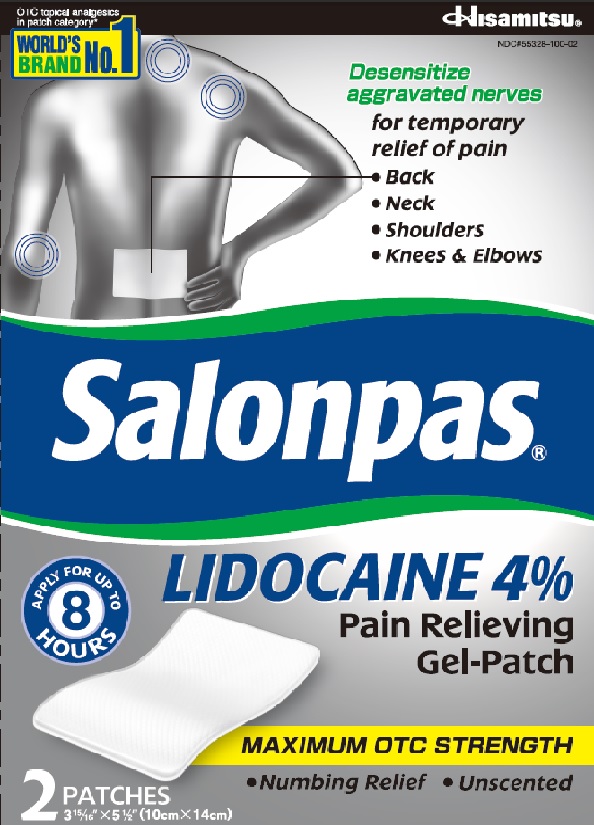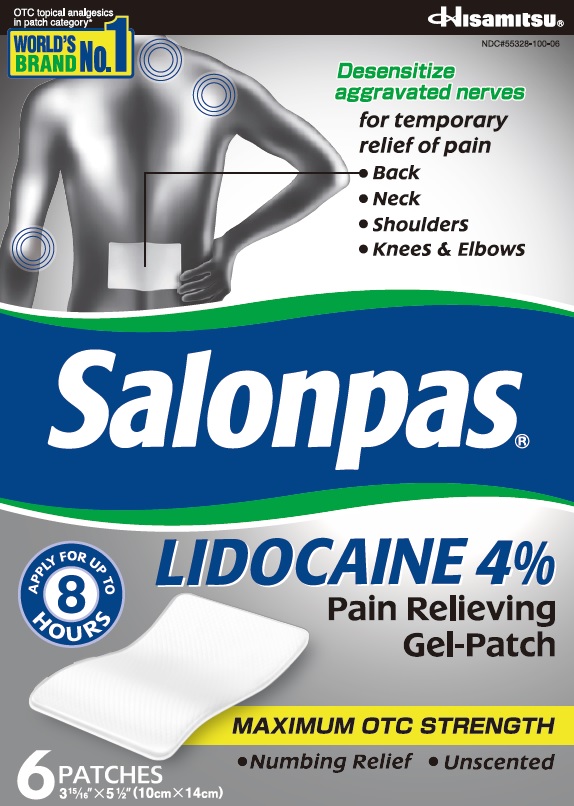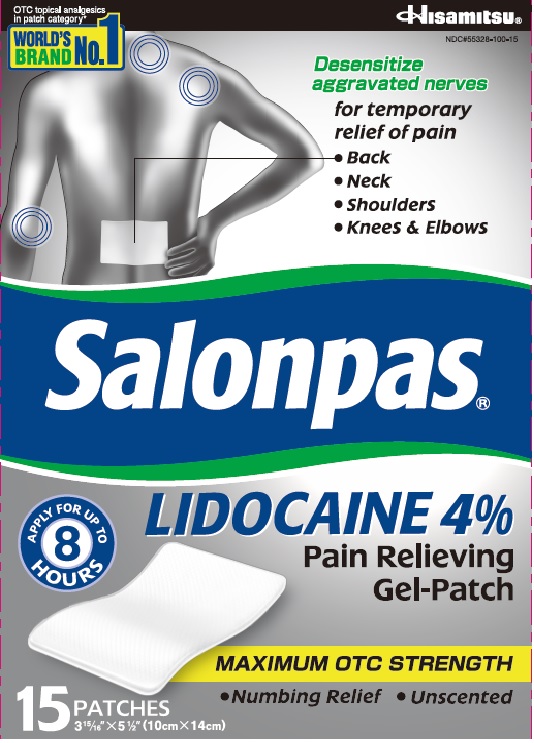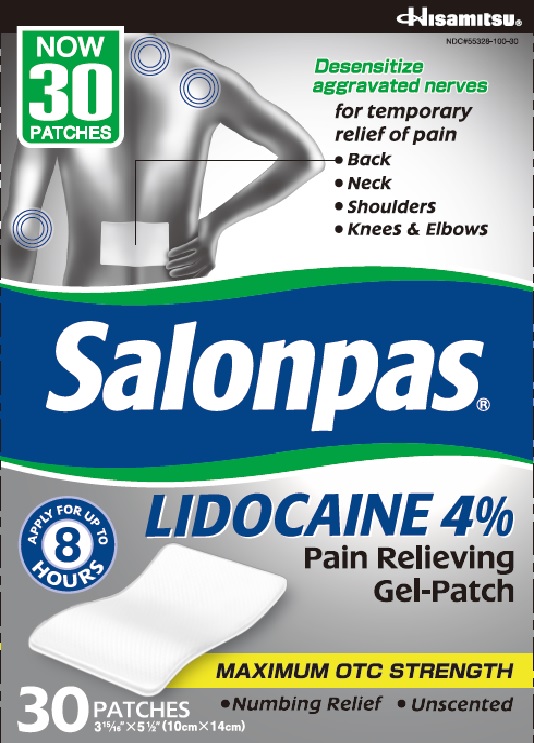 DRUG LABEL: Salonpas LIDOCAINE Pain Relieving
NDC: 55328-100 | Form: PATCH
Manufacturer: Hisamitsu America, Inc.
Category: otc | Type: HUMAN OTC DRUG LABEL
Date: 20251223

ACTIVE INGREDIENTS: LIDOCAINE 560 mg/1 1
INACTIVE INGREDIENTS: ALUMINUM SILICATE; DIHYDROXYALUMINUM AMINOACETATE; EDETATE DISODIUM; GELATIN; GLYCERIN; METHYLPARABEN; OLEIC ACID; PROPYLENE GLYCOL; PROPYLPARABEN; TARTARIC ACID; TITANIUM DIOXIDE; WATER

Active ingredient

Lidocaine 4%

Purpose

Topical anesthetic

Uses

For temporary relief of pain

Warnings

For external use only

Do not use

● more than 1 patch at a time

● on wounds or damaged skin

● with a heating pad

● if you are allergic to any ingredients of this product

When using this product

● use only as directed

● avoid contact with the eyes, mucous membranes or rashes

● do not bandage tightly

Stop use and ask a doctor if

● localized skin reactions occur, such as rash, itching, redness, irritation, pain, swelling and blistering

● conditions worsen

● symptoms persist for more than 7 days

● symptoms clear up and occur again within a few days

If pregnant or breast-feeding,

ask a health professional before use.

Keep out of reach of children.

If swallowed, get medical help or contact a Poison Control Center right away.

Directions

Adults and children 12 years of age and over:

● clean and dry affected area

● remove film from patch and apply to the skin (see illustration)

● apply 1 patch at a time to affected area, not more than 3 to 4 times daily

● remove patch from the skin after at most 8-hour application

Children under 12 years of age: consult a doctor

Other information

● Avoid storing product in direct sunlight

● Protect product from excessive moisture

Inactive ingredients

aluminum silicate, dihydroxyaluminum aminoacetate, disodium edetate, gelatin, glycerin, methylparaben, oleic acid, polyacrylic acid, polyvinyl alcohol, propylene glycol, propylparaben, sodium polyacrylate, tartaric acid, titanium dioxyde, water

Questions or comments?

Toll free 1-800-826-8861 www.salonpas.us

Principal Display Panel

OTC topical analgesics in patch category*

WORLD'S BRAND NO.1

Hisamitsu

NDC#55328-100-02

Desensitize aggravated nerves

for temprary relief of pain

● Back

● Neck

● Shoulders

● Knees & Elbows

Salonpas LIDOCAINE 4% Pain Relieving Gel-Patch

APPLY FOR UP TO 8 HOURS

MAXIMUM OTC STRENGTH

● Numbing Relief

● Unscented

2 PATCHES

3 15/16'' X 5 1/2'' (10cm X 14cm)

Principal Display Panel

OTC topical analgesics in patch category*

WORLD'S BRAND NO.1

Hisamitsu

NDC#55328-100-06

Desensitize aggravated nerves

for temprary relief of pain

● Back

● Neck

● Shoulders

● Knees & Elbows

Salonpas LIDOCAINE 4% Pain Relieving Gel-Patch

APPLY FOR UP TO 8 HOURS

MAXIMUM OTC STRENGTH

● Numbing Relief

● Unscented

6 PATCHES

3 15/16'' X 5 1/2'' (10cm X 14cm)

Principal Display Panel

OTC topical analgesics in patch category*

WORLD'S BRAND NO.1

Hisamitsu

NDC#55328-100-15

Desensitize aggravated nerves

for temprary relief of pain

● Back

● Neck

● Shoulders

● Knees & Elbows

Salonpas LIDOCAINE 4% Pain Relieving Gel-Patch

APPLY FOR UP TO 8 HOURS

MAXIMUM OTC STRENGTH

● Numbing Relief

● Unscented

15 PATCHES

3 15/16'' X 5 1/2'' (10cm X 14cm)

Principal Display Panel

NOW 30 PATCHES

Hisamitsu

NDC#55328-100-30

Desensitize aggravated nerves

for temprary relief of pain

● Back

● Neck

● Shoulders

● Knees & Elbows

Salonpas LIDOCAINE 4% Pain Relieving Gel-Patch

APPLY FOR UP TO 8 HOURS

MAXIMUM OTC STRENGTH

● Numbing Relief

● Unscented

30 PATCHES

3 15/16'' X 5 1/2'' (10cm X 14cm)

Principal Display Panel

CUT OPEN HERE

Hisamitsu

NDC#55328-100-01

HOW TO APPLY

Fold sides back, pull apart to expose adhesive.

Place on affected area.

Peel off one side of the film.

Peel off the remaining film.

Press and smooth patch to secure.

Salonpas LIDOCAINE 4% Pain Relieving Gel-Patch

APPLY FOR UP TO 8 HOURS

MAXIMUM OTC STRENGTH

● Numbing Relief

● Unscented

1 PATCH

3 15/16'' X 5 1/2'' (10cm X 14cm)

Scan for HOW TO APPLY Video